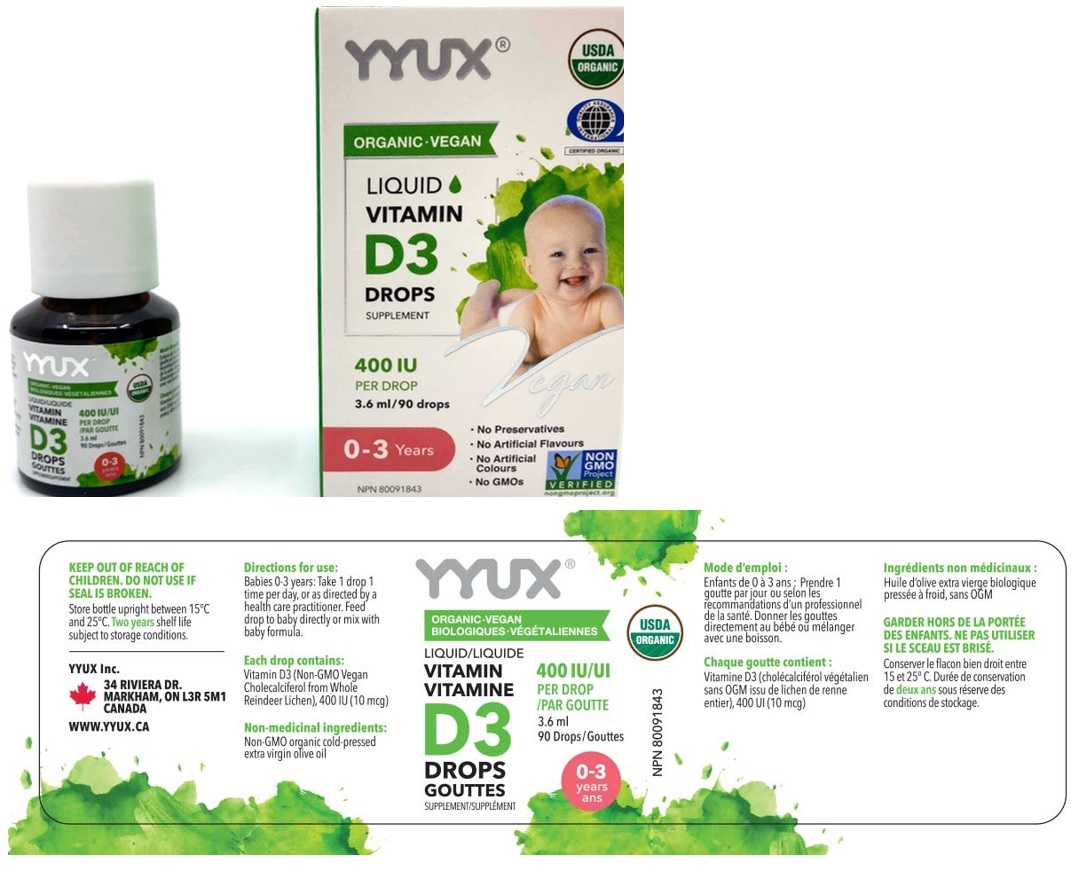 DRUG LABEL: YYUX Vegan Baby Liquid Vitamin D3 Drops 400 IU
NDC: 81303-540 | Form: SOLUTION/ DROPS
Manufacturer: Yyux Inc
Category: other | Type: DIETARY SUPPLEMENT
Date: 20201229

ACTIVE INGREDIENTS: CHOLECALCIFEROL 10 ug/0.04 mL
INACTIVE INGREDIENTS: OLIVE OIL

YYUX® ORGANIC - VEGAN LIQUID VITAMIN D3 DROPS SUPPLEMENT

Active Ingredient

Vitamin D3 (Cholecalciferol) 400IU (10ug per drop)

Supplement Facts; Serving Size: 1 drop; Serving Per Container: 90
Amount Per Serving | DV%
Calories 0
Total Fat 0 g | <1%
Cholesterol 0 mg | 0%
Vitamin D3 (Cholecalciferol) 10mcg (400IU) | 100%
Other ingredients: Olive Oil

Non-medicinal ingredients: Non-GMO organic cold-pressed extra virgin olive oil

Warnings:

KEEP OUT OF REACH OF CHILDREN. DO NOT USE IF SEAL IS BROKEN.

Storage:

Store bottle upright between 15°C and 25°C. Two years shelf life subject to storage conditions.

Directions for use:

Babies 0-3 years: Take 1 drop 1 time per day, or a directed by a health care practitioner. Feed drop to baby directly or mix with baby formula.

A dropper supplied.

HEALTH CLAIM

Helps in the development and maintenance of bones and teeth. Helps in the absorption and use of calcium and phosphorus. Helps with immune function.

Each drop contains: Vitamin D3 (Non-GMO Vegan Cholecalciferol from Whole Reindeer Lichen), 400 IU (10 mcg)

USDA ORGANIC

QUALITY ASSURANCE INTERNATIONAL

CERTIFIED ORGANIC

NON GMO Project VERIFIED

nongmoproject.org

0-3 Years

• No Preservatives

• No Artificial Flavours

• No Artificial Colours

• No GMOs
YYUX Inc.
34 RIVIERA DR.
MARKHAM, ON L3R 5M1
CANADAWWW.YYUX.CA